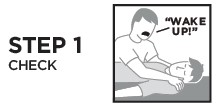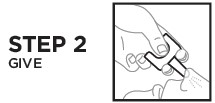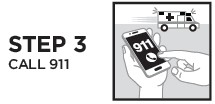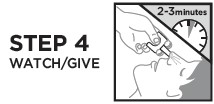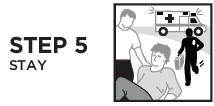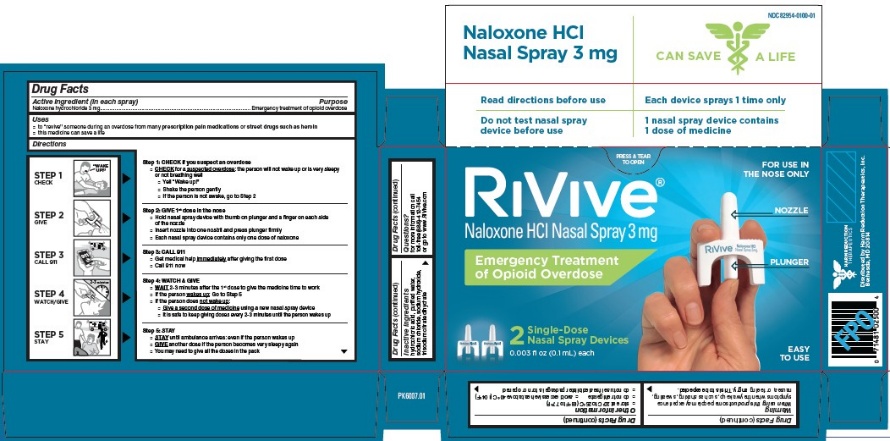 DRUG LABEL: RiVive
NDC: 82954-0100 | Form: SPRAY
Manufacturer: Harm Reduction Therapeutics, Inc.
Category: otc | Type: HUMAN OTC DRUG LABEL
Date: 20260113

ACTIVE INGREDIENTS: NALOXONE HYDROCHLORIDE 3 mg/0.1 mL
INACTIVE INGREDIENTS: HYDROCHLORIC ACID; WATER; SODIUM CHLORIDE; SODIUM HYDROXIDE; TRISODIUM CITRATE DIHYDRATE

RiVive®
Naloxone HCl Nasal Spray 3 mg
Emergency Treatment of Opioid Overdose

Active ingredient (in each spray)

Naloxone hydrochloride 3 mg

Purpose

Emergency treatment of opioid overdose

Uses

- to “revive” someone during an overdose from many prescription pain medications or street drugs such as heroin
- this medicine can save a life

Directions

Step 1: CHECK if you suspect an overdose

- CHECK for a suspected overdose: the person will not wake up or is very sleepy or not breathing well
- Yell “Wake up!”
- Shake the person gently
- If the person is not awake, go to Step 2

Step 2: GIVE 1st dose in the nose

- Hold nasal spray device with thumb on plunger and a finger on each side of the nozzle
- Insert nozzle into one nostril and press plunger firmly
- Each nasal spray device contains only one dose of naloxone

Step 3: CALL 911

- Get medical help immediately after giving the first dose
- Call 911 now

Step 4: WATCH & GIVE

- WAIT 2-3 minutes after the 1st dose to give the medicine time to work
- If the person wakes up: Go to Step 5
- If the person does not wake up:
  • Give a second dose of medicine using a new nasal spray device
  • It is safe to keep giving doses every 2-3 minutes until the person wakes up

Step 5: STAY

- STAY until ambulance arrives: even if the person wakes up
- GIVE another dose if the person becomes very sleepy again
- You may need to give all the doses in the pack

Warning

When using this product some people may experience symptoms when they wake up, such as shaking, sweating, nausea, or feeling angry. This is to be expected.

Other information

- store at 20ºC to 25ºC (68ºF to 77ºF)
- do not refrigerate
- avoid excessive heat above 40ºC (104ºF)
- do not use if sealed blister package is torn or opened

Inactive ingredients

hydrochloric acid, purified water, sodium chloride, sodium hydroxide, trisodium citrate dihydrate

Questions?

for more information call toll-free (888)-412-7454 or go to www.RiVive.com

Package/Label Principal Display Panel

RiVive®
Naloxone HCl Nasal Spray 3 mg
Emergency Treatment
of Opioid Overdose
FOR USE IN
THE NOSE ONLY
NOZZLE
PLUNGER
EASY
TO USE
2-Single-Dose
Nasal Spray Devices
0.003 fl oz (0.1 mL) each

HARM REDUCTION
THERAPEUTICS
Distributed by Harm Reduction Therapeutics, Inc.
Bethesda, MD 20814

Label